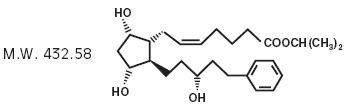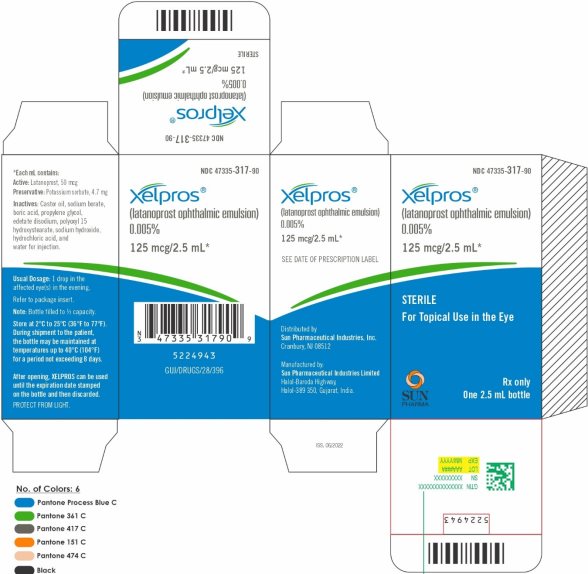 DRUG LABEL: XELPROS
NDC: 47335-317 | Form: SOLUTION/ DROPS
Manufacturer: Sun Pharmaceutical Industries, Inc.
Category: prescription | Type: HUMAN PRESCRIPTION DRUG LABEL
Date: 20251218

ACTIVE INGREDIENTS: LATANOPROST 0.05 mg/1 mL
INACTIVE INGREDIENTS: POTASSIUM SORBATE 4.70 mg/1 mL; BORIC ACID 3.00 mg/1 mL; EDETATE DISODIUM 3.00 mg/1 mL; CASTOR OIL 1.5 mg/1 mL; POLYOXYL 15 HYDROXYSTEARATE 2.5 mg/1 mL; PROPYLENE GLYCOL 15 mg/1 mL; SODIUM BORATE 1.1 mg/1 mL; HYDROCHLORIC ACID; SODIUM HYDROXIDE; WATER

HIGHLIGHTS OF PRESCRIBING INFORMATION

These highlights do not include all the information needed to use XELPROS safely and effectively. See full prescribing information for XELPROS.
XELPROS® (latanoprost ophthalmic emulsion) 0.005%, for topical ophthalmic use
Initial U.S. Approval: 1996

1 INDICATIONS AND USAGE

XELPROS is a prostaglandin F2α analog indicated for reduction of elevated intraocular pressure in patients with open-angle glaucoma, or ocular hypertension. (1)

2 DOSAGE AND ADMINISTRATION

One drop in the affected eye(s) once daily in the evening. (2)

3 DOSAGE FORMS AND STRENGTHS

Ophthalmic emulsion containing latanoprost 50 mcg/mL (0.005%). (3)

4 CONTRAINDICATIONS

Known hypersensitivity to latanoprost or any other ingredients in this product. (4)

5 WARNINGS AND PRECAUTIONS

- Pigmentation: Pigmentation of the iris, periorbital tissue (eyelid) and eyelashes can occur. Iris pigmentation likely to be permanent. (5.1)
- Eyelash Changes: Gradual change to eyelashes including increased length, thickness and number of lashes. Usually reversible. (5.2)

6 ADVERSE REACTIONS

Most common ocular adverse reactions (incidence ≥5%) for XELPROS are: eye pain/stinging, ocular hyperemia, conjunctival hyperemia, eye discharge, growth of eyelashes, and eyelash thickening. (6.1)
To report SUSPECTED ADVERSE REACTIONS, contact Sun Pharmaceutical Industries, Inc. at 1-800-818-4555 or FDA at 1-800-FDA-1088 or www.fda.gov/medwatch.

7 DRUG INTERACTIONS

Thimerosal: Precipitation may occur if drugs containing thimerosal are used concomitantly with XELPROS. If such drugs are used, they should be administered at least five (5) minutes apart. (7)

FULL PRESCRIBING INFORMATION

1 INDICATIONS AND USAGE

XELPROS (latanoprost ophthalmic emulsion) 0.005% is indicated for the reduction of elevated intraocular pressure (IOP) in patients with open-angle glaucoma or ocular hypertension.

2 DOSAGE AND ADMINISTRATION

The recommended dosage is one drop in the affected eye(s) once daily in the evening. If one dose is missed, treatment should continue with the next dose as normal.

The dosage of XELPROS should not exceed once daily; the combined use of two or more prostaglandins, or prostaglandin analogs including XELPROS is not recommended. It has been shown that administration of these prostaglandin drug products more than once daily may decrease the intraocular pressure (IOP) lowering effect or cause paradoxical elevations in IOP.

Reduction of the intraocular pressure starts approximately 3 to 4 hours after administration and the maximum effect is reached after 8 to 12 hours.

XELPROS may be used concomitantly with other topical ophthalmic drug products to lower intraocular pressure. If more than one topical ophthalmic drug is being used, the drugs should be administered at least five (5) minutes apart. Contact lenses should be removed prior to the administration of XELPROS, and may be reinserted 15 minutes after administration.

3 DOSAGE FORMS AND STRENGTHS

Ophthalmic emulsion containing latanoprost 50 mcg/mL (0.005%).

4 CONTRAINDICATIONS

Known hypersensitivity to latanoprost, or any other ingredients in this product.

5 WARNINGS AND PRECAUTIONS

5.1 Pigmentation

Topical latanoprost ophthalmic products, including XELPROS, have been reported to cause changes to pigmented tissues. The most frequently reported changes have been increased pigmentation of the iris, periorbital tissue (eyelid) and eyelashes. Pigmentation is expected to increase as long as latanoprost is administered.

The pigmentation change is due to increased melanin content in the melanocytes rather than to an increase in the number of melanocytes. After discontinuation of latanoprost, pigmentation of the iris is likely to be permanent, while pigmentation of the periorbital tissue and eyelash changes have been reported to be reversible in some patients. Patients who receive treatment should be informed of the possibility of increased pigmentation. The long-term effects of increased pigmentation are not known.

Iris color change may not be noticeable for several months to years. Typically, the brown pigmentation around the pupil spreads concentrically towards the periphery of the iris and the entire iris or parts of the iris become more brownish. Neither nevi nor freckles of the iris appear to be affected by treatment. While treatment with XELPROS can be continued in patients who develop noticeably increased iris pigmentation, these patients should be examined regularly.

5.2 Eyelash Changes

Latanoprost ophthalmic products, including XELPROS, may gradually change eyelashes and vellus hair in the treated eye; these changes include increased length, thickness, pigmentation, the number of lashes or hairs, and misdirected growth of eyelashes. Eyelash changes are usually reversible upon discontinuation of treatment.

5.3 Intraocular Inflammation

XELPROS should be used with caution in patients with a history of intraocular inflammation (iritis/uveitis) and should generally not be used in patients with active intraocular inflammation because inflammation may be exacerbated.

5.4 Macular Edema

Macular edema, including cystoid macular edema, has been reported during treatment with latanoprost ophthalmic products, including XELPROS. XELPROS should be used with caution in aphakic patients, in pseudophakic patients with a torn posterior lens capsule, or in patients with known risk factors for macular edema.

5.5 Herpetic Keratitis

Reactivation of herpes simplex keratitis has been reported during treatment with latanoprost. XELPROS should be used with caution in patients with a history of herpetic keratitis. XELPROS should be avoided in cases of active herpes simplex keratitis because inflammation may be exacerbated.

5.6 Bacterial Keratitis

There have been reports of bacterial keratitis associated with the use of multiple-dose containers of topical ophthalmic products. These containers had been inadvertently contaminated by patients who, in most cases, had a concurrent corneal disease or a disruption of the ocular epithelial surface.

5.7 Contact Lens Use

Contact lenses should be removed prior to the administration of XELPROS and may be reinserted 15 minutes after administration.

6 ADVERSE REACTIONS

6.1 Clinical Trials Experience

Because clinical trials are conducted under widely varying conditions, adverse reaction rates observed in the clinical studies of a drug cannot be directly compared to rates in the clinical studies of another drug and may not reflect the rates observed in clinical practice.

Across multiple clinical trials conducted with XELPROS (latanoprost ophthalmic emulsion) 0.005%, the most frequently reported ocular adverse reactions were eye pain/stinging upon instillation and ocular hyperemia, reported in 55% and 41% of XELPROS treated patients, respectively (Table 1). Less than 1% of patients discontinued therapy because of intolerance to the eye pain/stinging or to the ocular hyperemia.

Table 1. Ocular Adverse Reactions Reported by ≥ 1% of Subjects Receiving XELPROS

System Organ Class/ Preferred Term | XELPROS (N = 448)
Eye disorders | 325 (73%)
Eye pain / stinging | 246 (55%)
Ocular hyperemia | 185 (41%)
Conjunctival hyperemia | 65 (15%)
Eye discharge | 53 (12%)
Growth of eyelashes | 47 (11%)
Eyelash thickening | 35 (8%)
Ocular Itching | 20 (5%)
Visual acuity reduced | 16 (4%)
Dry eye | 13 (3%)
Erythema of eyelid | 14 (3%)
Foreign body sensation in eyes | 9 (2%)
Eyelid edema | 7 (2%)
Punctate keratitis | 6 (1%)
Eyelash discoloration | 5 (1%)
Conjunctival edema | 5 (1%)

6.2 Postmarketing Experience

The following reactions have been identified during postmarketing use of topical latanoprost products in clinical practice. Because they are reported voluntarily from a population of unknown size, it is not always possible to reliably estimate their frequency or establish a causal relationship to drug exposure.

The reactions, which have been chosen for inclusion due to either their seriousness, frequency of reporting, possible causal connection to latanoprost ophthalmic emulsion or a combination of these factors, include:

- Nervous System Disorders: Dizziness, headache, toxic epidermal necrolysis
- Eye Disorders: Corneal edema and erosions; intraocular inflammation (iritis/uveitis); macular edema, including cystoid macular edema; trichiasis; periorbital and lid changes resulting in deepening of the eyelid sulcus; iris cyst; eyelid skin darkening; localized skin reaction on the eyelids; conjunctivitis; pseudopemphigoid of the ocular conjunctiva
- Respiratory, Thoracic and Mediastinal Disorders: Asthma and exacerbation of asthma; dyspnea
- Gastrointestinal Disorders: Nausea; vomiting
- Skin and Subcutaneous Tissue Disorders: Pruritus
- Infections and Infestations: Herpes keratitis
- Cardiac Disorders: Angina; palpitations; angina unstable
- General Disorders and Administration Site Conditions: Chest pain

7 DRUG INTERACTIONS

In vitro studies have shown that precipitation occurs when eye drops containing thimerosal are mixed with XELPROS. If such drugs are used, they should be administered at least five (5) minutes apart.

The combined use of two or more prostaglandins, or prostaglandin analogs including XELPROS is not recommended. It has been shown that administration of these prostaglandin drug products more than once daily may decrease the IOP lowering effect or cause paradoxical elevations in IOP.

8 USE IN SPECIFIC POPULATIONS

8.1 Pregnancy

Risk Summary

There are no adequate and well-controlled studies of XELPROS ophthalmic emulsion in pregnant women to inform drug-associated risks.

In animal reproduction studies, intravenous (IV) administration of latanoprost to pregnant rabbits and rats throughout the period of organogenesis produced malformations, embryofetal lethality and spontaneous abortion at clinically relevant doses [see Data].

The background risk of major birth defects and miscarriage for the indicated population is unknown. However, the background risk in the U.S. general population of major birth defects is 2 to 4%, and of miscarriage is 15 to 20% of clinically recognized pregnancies.

Data

Animal Data

Embryofetal studies were conducted in pregnant rabbits administered latanoprost daily by IV injection on gestation days 6 through 18, to target the period of organogenesis. A no observed adverse effect level (NOAEL) was not established for rabbit developmental toxicity. Post-implantation loss due to late resorption was shown as doses ≥ 0.2 mcg/kg/day (equivalent to 1.3 times the maximum recommended human ophthalmic dose [RHOD], on a mg/m^2 basis, assuming 100% absorption). Spina bifida and abortion occurred at 5 mcg/kg/day (equivalent to 32 times the maximum RHOD). Total litter loss due to early resorption was observed at doses ≥ 50 mcg/kg/day (324 times the maximum RHOD). Transient signs of maternal toxicity were observed after IV dosing (increased breathing, muscle tremors, slight motor incoordination) at 300 mcg/kg/day (1946 times the maximum RHOD). No maternal toxicity was observed at doses up to 50 mcg/kg/day.

Embryofetal studies were conducted in pregnant rats administered latanoprost daily by IV injection on gestation days 6 through 15, to target the period of organogenesis. A NOAEL for rat developmental toxicity was not established. Cleft palate was observed at 1 mcg/kg (equivalent to 3.2 times the maximum RHOD, on a mg/m^2 basis, assuming 100% absorption). Brain porencephalic cyst(s) were observed ≥50 mcg/kg (162 times the maximum RHOD). Skeletal anomalies were observed at 250 mcg/kg (811 times the maximum RHOD). No maternal toxicity was detectable at 250 mcg/kg/day.

Prenatal and postnatal development was assessed in rats. Pregnant rats were administered latanoprost daily by IV injection from gestation day 15, through delivery, until weaning (lactation Day 21). No adverse effects on rat offspring were observed at doses up to 10 mcg/kg/day (32 times the maximum RHOD, on a mg/m^2 basis, assuming 100% absorption). At 100 mcg/kg/day (324 times the maximum RHOD), maternal deaths and pup mortality occurred.

8.2 Lactation

Risk Summary

It is not known whether this drug or its metabolites are excreted in human milk. Because many drugs are excreted in human milk, caution should be exercised when XELPROS is administered to a nursing woman.

The developmental and health benefits of breastfeeding should be considered along with the mother’s clinical need for XELPROS and any potential adverse effects on the breastfed child from XELPROS.

8.4 Pediatric Use

Safety and effectiveness in pediatric patients have not been established.

8.5 Geriatric Use

No overall differences in safety or effectiveness have been observed between elderly and younger patients.

10 OVERDOSAGE

Intravenous infusion of up to 3 mcg/kg of latanoprost in healthy volunteers produced mean plasma concentrations 200 times higher than during clinical treatment with XELPROS and no adverse reactions were observed. Intravenous dosages of 5.5 to 10 mcg/kg caused abdominal pain, dizziness, fatigue, hot flashes, nausea, and sweating.

If overdosage with XELPROS occurs, treatment should be symptomatic.

11 DESCRIPTION

Latanoprost is a prostaglandin F2α analogue. Its chemical name is isopropyl-(Z)-7[(1R,2R,3R,5S)3,5-dihydroxy-2-[(3R)-3-hydroxy-5-phenylpentyl]cyclopentyl]-5-heptenoate. Its molecular formula is C26H40O5 and its chemical structure is:

Latanoprost is a pale yellow to yellow viscous oil that is very soluble in acetonitrile and freely soluble in acetone, ethanol, ethyl acetate, isopropanol, methanol, and octanol. It is practically insoluble in water.

XELPROS (latanoprost ophthalmic emulsion) 0.005% is a sterile, isotonic, buffered aqueous emulsion of latanoprost with a pH approximately 7.0 and an osmolality of approximately 375mOsmol/kg. Each mL of XELPROS contains 50 micrograms of latanoprost. Potassium sorbate 0.47% is added as a preservative. The inactive ingredients are: castor oil, sodium borate, boric acid, propylene glycol, edetate disodium, polyoxyl 15 hydroxystearate, sodium hydroxide, hydrochloric acid, and water for injection. One drop contains approximately 1.5 mcg of latanoprost.

12 CLINICAL PHARMACOLOGY

12.1 Mechanism of Action

Latanoprost is a prostaglandin F2α analogue that is believed to reduce the intraocular pressure (IOP) by increasing the outflow of aqueous humor. Studies in animals and man suggest that the main mechanism of action is increased uveoscleral outflow. Elevated IOP represents a major risk factor for glaucomatous field loss. The higher the level of IOP, the greater the likelihood of optic nerve damage and visual field loss.

12.2 Pharmacodynamics

Reduction of the IOP in man starts about 3-4 hours after administration and maximum effect is reached after 8-12 hours. IOP reduction is present for at least 24 hours.

12.3 Pharmacokinetics

Absorption

Latanoprost is absorbed through the cornea where the isopropyl ester prodrug is hydrolyzed to the acid form to become biologically active.

Distribution

The distribution volume in humans is 0.16 ± 0.02 L/kg. The acid of latanoprost can be measured in aqueous humor during the first 4 hours, and in plasma only during the first hour after local administration. Studies in man indicate that the peak concentration in the aqueous humor is reached about 2 hours after topical administration.

Elimination

Metabolism

Latanoprost, an isopropyl ester prodrug, is hydrolyzed by esterases in the cornea to the biologically active acid. The active acid of latanoprost reaching the systemic circulation is primarily metabolized by the liver to the 1,2-dinor and 1,2,3,4- tetranor metabolites via fatty acid β-oxidation.

Excretion

The elimination of the acid of latanoprost from human plasma is rapid (t1/2 =17 min) after both intravenous and topical administration. Systemic clearance is approximately 7 mL/min/kg. Following hepatic β-oxidation, the metabolites are mainly eliminated via the kidneys. Approximately 88% and 98% of the administered dose are recovered in the urine after topical and intravenous dosing, respectively.

13 NONCLINICAL TOXICOLOGY

13.1 Carcinogenesis, Mutagenesis, Impairment of Fertility

Carcinogenesis

Latanoprost was not carcinogenic in either mice or rats when administered by oral gavage at doses of up to 170 mcg/kg/day (approximately 2,800 times the recommended maximum human dose) for up to 20 and 24 months, respectively.

Mutagenesis

Latanoprost was not mutagenic in bacteria, in mouse lymphoma, or in mouse micronucleus tests. Chromosome aberrations were observed in vitro with human lymphocytes. Additional in vitro and in vivo studies on unscheduled DNA synthesis in rats were negative.

Impairment of Fertility

Latanoprost has not been found to have any effect on male or female fertility in rat studies at IV doses up to 250 mcg/kg/day (811 times the maximum RHOD, on a mg/m^2 basis, assuming 100% absorption).

14 CLINICAL STUDIES

14.1 Elevated Baseline IOP

In randomized, controlled clinical trials of patients with open angle glaucoma or ocular hypertension with mean baseline IOP of 23 - 26 mmHg, the mean IOP-lowering effect of XELPROS administered once daily in the evening was up to 6 - 8 mmHg.

16 HOW SUPPLIED/STORAGE AND HANDLING

XELPROS (latanoprost ophthalmic emulsion) is supplied as an off-white to pale yellow, translucent, isotonic, sterile, buffered emulsion of latanoprost 0.005% (50 mcg/mL). It is supplied as a 2.5 mL emulsion filled in a 5-mL clear low density polyethylene bottle with a clear low density polyethylene dropper tip, and a turquoise high density polyethylene pilfer-proof cap. Each mL contains 50 mcg of latanoprost.

2.5 mL fill, 0.005% (50 mcg/mL)

Package of 1 bottle NDC 47335-317-90

Multi-Pack of 3 bottles NDC 47335-317-92

Storage: Protect from light. Store at 2°C to 25°C (36°F to 77°F). During shipment to the patient, the bottle may be maintained at temperatures up to 40°C (104°F) for a period not exceeding 8 days. After opening, XELPROS can be used until the expiration date stamped on bottle and then discarded.

17 PATIENT COUNSELING INFORMATION

Potential for Pigmentation

Advise patients about the potential for increased brown pigmentation of the iris, which may be permanent. Patients should also be informed about the possibility of eyelid skin darkening, which may be reversible after discontinuation of XELPROS [see Warnings and Precautions (5.1)].

Potential for Eyelash Changes

Inform patients of the possibility of eyelash and vellus hair changes in the treated eye during treatment with latanoprost ophthalmic emulsion. These changes may result in a disparity between eyes in length, thickness, pigmentation, number of eyelashes or vellus hairs, and/or direction of eyelash growth. Eyelash changes are usually reversible upon discontinuation of treatment.

Handling the Container

Instruct patients to avoid allowing the tip of the dispensing container to contact the eye or surrounding structures because this could cause the tip to become contaminated by common bacteria known to cause ocular infections. Serious damage to the eye and subsequent loss of vision may result from using contaminated emulsions [see Warnings and Precautions (5.6)].

When to Seek Physician Advice

Advise patients that if they develop an intercurrent ocular condition (e.g., trauma or infection) or have ocular surgery, or develop any ocular reactions, particularly conjunctivitis and eyelid reactions, they should immediately seek their physician’s advice concerning the continued use of the multiple-dose container.

Contact Lens Use

Advise patients that contact lenses should be removed prior to administration of the emulsion. Lenses may be reinserted 15 minutes following administration of XELPROS.

Use with Other Ophthalmic Drugs

Advise patients that if more than one topical ophthalmic drug is being used, the drugs should be administered at least five (5) minutes apart.

If a Dose is Missed

Advise patients that if one dose is missed, treatment should continue with the next dose as normal.

Manufactured by:

Sun Pharmaceutical Industries Limited

Halol-Baroda Highway,

Halol- 389-350, Gujarat, India.

Distributed by:

Sun Pharmaceutical Industries, Inc.

Cranbury, NJ 08512

5XXXXXX

ISS. 09/2024